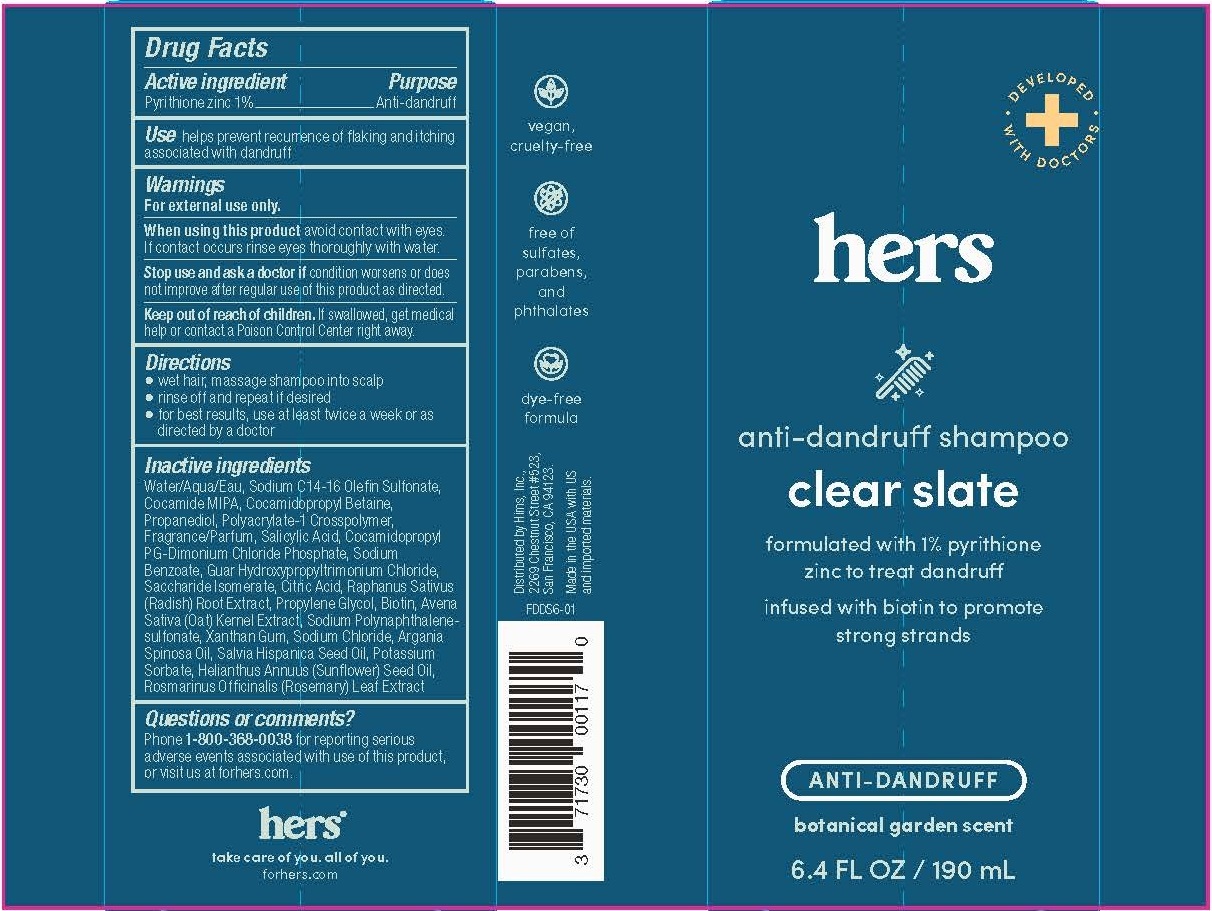 DRUG LABEL: Clear Slate
NDC: 71730-020 | Form: SHAMPOO
Manufacturer: Hims Inc
Category: otc | Type: HUMAN OTC DRUG LABEL
Date: 20231101

ACTIVE INGREDIENTS: PYRITHIONE ZINC 1 g/100 mL
INACTIVE INGREDIENTS: COCO MONOISOPROPANOLAMIDE; RADISH; PROPYLENE GLYCOL; ROSEMARY; WATER; SODIUM C14-16 OLEFIN SULFONATE; COCAMIDOPROPYL BETAINE; PROPANEDIOL; SALICYLIC ACID; COCAMIDOPROPYL PG-DIMONIUM CHLORIDE PHOSPHATE; SODIUM BENZOATE; GUAR HYDROXYPROPYLTRIMONIUM CHLORIDE (1.7 SUBSTITUENTS PER SACCHARIDE); CITRIC ACID MONOHYDRATE; OAT; FORMALDEHYDE/SODIUM NAPHTHALENESULFONATE COPOLYMER (3000 MW); SUNFLOWER OIL; XANTHAN GUM; POLYACRYLATE-1 CROSSPOLYMER; SODIUM CHLORIDE; ARGAN OIL; SACCHARIDE ISOMERATE; BIOTIN; CHIA SEED OIL; POTASSIUM SORBATE

hers anti-danruff shampoo - clear slate

Active ingredient

Pyrithione zinc 1%

Purpose

Anti-dandruff

Use

helps prevent recurrence of flaking and itching associated with dandruff

Warnings

For external use only

When using this product avoid contact with eyes. If contact occurs rinse eyes thoroughly with water.

Stop use and ask a doctor if condition worsens or does not improve after regular use of this product as directed.

Keep out of reach of children. If swallowed, get medical help or contact a Poison Control Center right away.

Directions

- wet hair, massage shampoo into scalp
- rinse off and repeat if desired
- for best results, use at least twice a week or as directed by a doctor

Inactive ingredients

WaterAqua/Eau, Sodium C14-16 Olefin Sulfonate, Cocamide MIPA, Cocamidopropyl Betaine, Propanediol, Polyacrylate-1 Crosspolymer, Fragrance/Parfum, Salicylic Acid, Cocamidopropyl PG-Dimonium Chloride Phosphate, Sodium Benzoate, Guar Hydroxypropyltrimonium Chloride, Saccharide Isomerate, Citric Acid, Raphanus Sativus (Radish) Root Extract, Propylene Glycol, Biotin, Avena Sativa (Oat) Kernel Extract, Sodium Polynaphthalene-sulfonate, Xanthan Gum, Sodium Chloride, Argania Spinosa Oil, Salvia Hispanica Seed Oil, Potassium Sorbate, Helianthus Annuus (Sunflower) Seed Oil, Rosmarinus Officinalis (Rosemary) Leaf Extract

Questions or comments?

Phone 1-800-368-0038 for reporting serious adverse events associated with use of this product, or visit us at forhers.com

PACKAGE LABEL

hers

anti-dandruff shampoo

clear slate

formulated with 1% pyrithione zinc to treat dandruff

infused with biotin to promote strong strands

ANTI-DANDRUFF

botanical garden scent

6.4 FL OZ / 190 mL

Distributed by Hims, Inc.

2269 Chestnut Street #523

San Francisco, CA 94123

Made in the USA with US and imported materials.